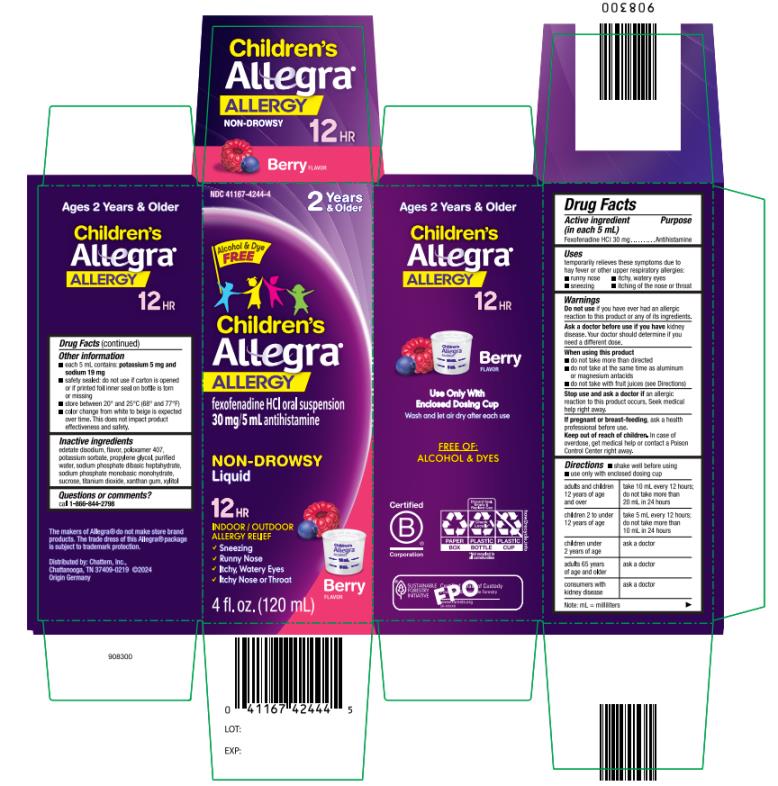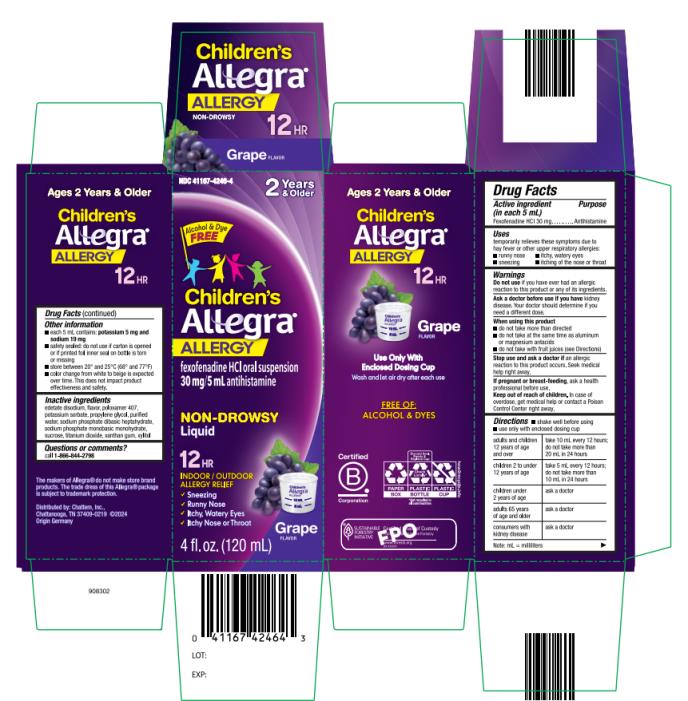 DRUG LABEL: Childrens Allegra Allergy
NDC: 41167-4244 | Form: SUSPENSION
Manufacturer: Chattem, Inc.
Category: otc | Type: HUMAN OTC DRUG LABEL
Date: 20241001

ACTIVE INGREDIENTS: FEXOFENADINE HYDROCHLORIDE 30 mg/5 mL
INACTIVE INGREDIENTS: EDETATE DISODIUM; POLOXAMER 407; PROPYLENE GLYCOL; WATER; SODIUM PHOSPHATE, DIBASIC, HEPTAHYDRATE; SODIUM PHOSPHATE, MONOBASIC, MONOHYDRATE; SUCROSE; TITANIUM DIOXIDE; XANTHAN GUM; POTASSIUM SORBATE; XYLITOL

Childrens Allegra Allergy Oral Suspension

Drug Facts

Active ingredient

(in each 5 mL)

Fexofenadine HCI 30 mg

Purpose

Antihistamine

Uses

temporarily relieves these symptoms due to hay fever or other upper respiratory allergies:

- runny nose
- sneezing
- itchy, water eyes
- itching of the nose or throat

Warnings

Do not use

if you have ever had an allergic reaction to this product or any of its ingredients.

Ask a doctor before use if you have

kidney disease. Your doctor should determine if you need a different dose.

When using this product

- do not take more than directed
- do not take at the same time as aluminum or magnesium antacids
- do not take with fruit juices (see Directions)

Stop use and ask a doctor if

an allergic reaction to this product occurs. Seek medical help right away.

If pregnant or breast-feeding,

ask a health professional before use.

Keep out of reach of children.

In case of overdose, get medical help or contact a Poison Control Center right away.

Directions

- shake well before using
- use only with enclosed dosing cup

adults and children 12 years of age and over | take 10 mL every 12 hours; do not take more than 20 mL in 24 hours
children 2 to under 12 years of age | take 5 mL every 12 hours; do not take more than 10 mL in 24 hours
children under 2 years of age | ask a doctor
adults 65 years of age and older | ask a doctor
consumers with kidney disease | ask a doctor

Note: mL = milliliters

Other information

- each 5 mL contains: each 5 mL contains: potassium 5 mg and sodium 19 mg
- safety sealed: do not use if carton is opened or if printed foil inner seal on bottle is torn or missing
- store between 20° and 25°C (68° and 77°F)
- color change from white to beige is expected over time. This does not impact product effectiveness and safety.

Inactive ingredients

edetate disodium, flavor, poloxamer 407, potassium sorbate, propylene glycol, purified water, sodium phosphate dibasic heptahydrate, sodium phosphate monobasic monohydrate, sucrose, titanium dioxide, xanthan gum, xylitol

Questions or comments?

call toll-free 1-800-844-2798

PRINCIPAL DISPLAY PANEL

NDC 41167-4244-4
Children’s
Allegra®
ALLERGY
fexofenadine HCI
oral suspension
12 HR
30 mg/5 ml antihistamine

PRINCIPAL DISPLAY PANEL

NDC 41167-4246-4
Children’s
Allegra®
ALLERGY
fexofenadine HCI
oral suspension
12 HR
30 mg/5 ml antihistamine